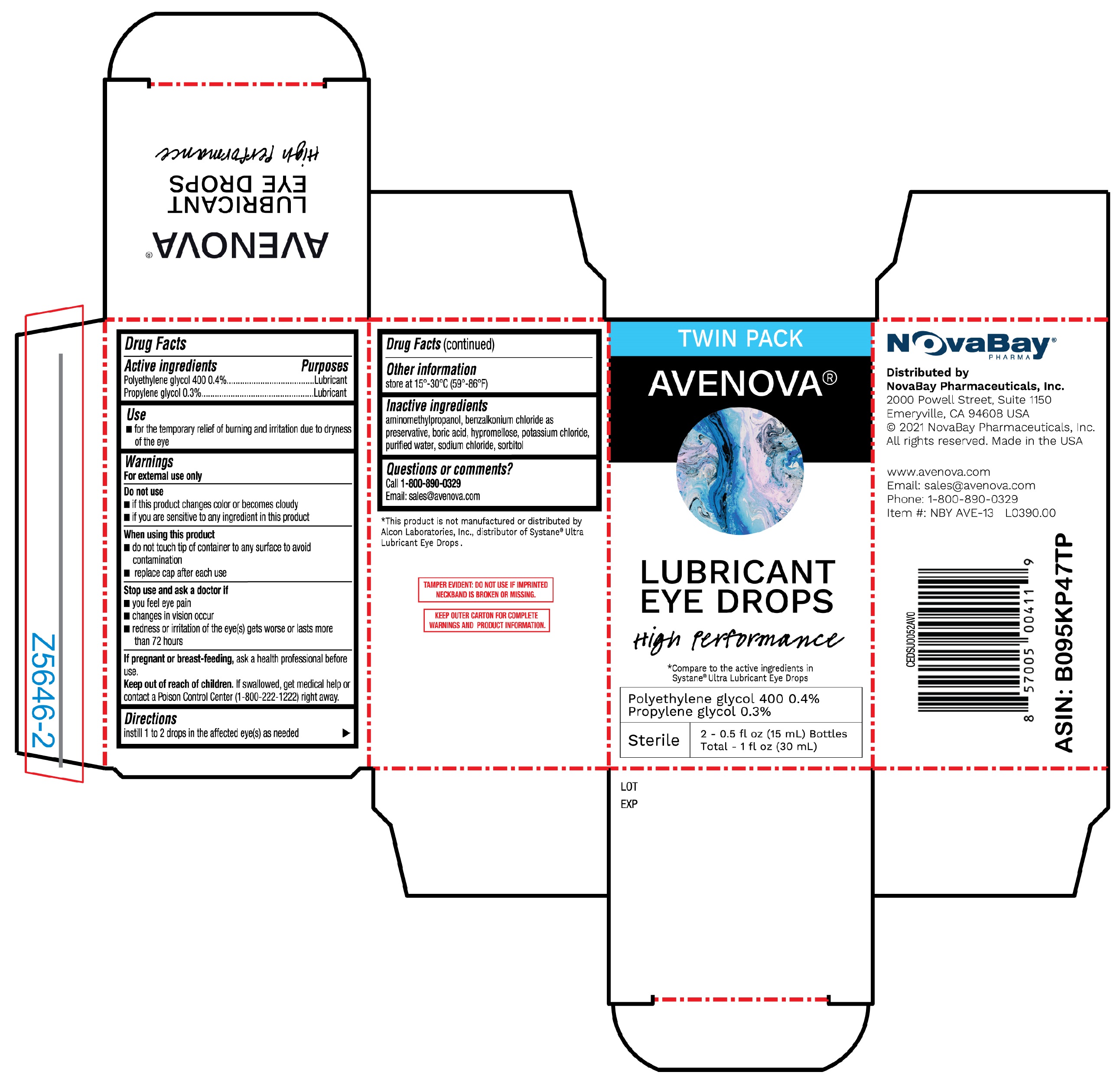 DRUG LABEL: Avenova Lubricant Eye Drops High Performance
NDC: 81963-101 | Form: SOLUTION/ DROPS
Manufacturer: NovaBay Pharmaceuticals, Inc.
Category: otc | Type: HUMAN OTC DRUG LABEL
Date: 20251230

ACTIVE INGREDIENTS: POLYETHYLENE GLYCOL 400 0.4 g/100 mL; PROPYLENE GLYCOL 0.3 g/100 mL
INACTIVE INGREDIENTS: WATER; BENZALKONIUM CHLORIDE; BORIC ACID; SODIUM CHLORIDE; SORBITOL; AMINOMETHYLPROPANOL; HYPROMELLOSE, UNSPECIFIED; POTASSIUM CHLORIDE

Avenova Lubricant Eye Drops High Performance 15mL twin pk (PLD)

Active ingredients

Polyethylene glycol 400 0.4%

Propylene glycol 0.3%

Purposes

Lubricant

Lubricant

Use

- for the temporary relief of burning and irritation due to dryness of the eye

Warnings

For external use only

Do not use

- if this product changes color or becomes cloudy
- if you are sensitive to any ingredient in this product

When using this product

- do not touch tip of container to any surface to avoid contamination
- replace cap after each use

Stop use and ask a doctor if

- you feel eye pain
- changes in vision occur
- redness or irritation of the eye(s) gets worse or lasts more than 72 hours

If pregnant or breast-feeding,

ask a health professional before use.

Keep out of reach of children.

If swallowed, get medical help or contact a Poison Control Center (1-800-222-1222) right away.

Directions

instill 1 to 2 drops in the affected eye(s) as needed

Other information

store at 15°-30°C (59°-86°F)

Inactive ingredients

aminomethylpropanol, benzalkonium chloride as preservative, boric acid, hypromellose, potassium chloride, purified water, sodium chloride, sorbitol

Questions or comments?

Call 1-800-890-0329

Email: sales@avenova.com